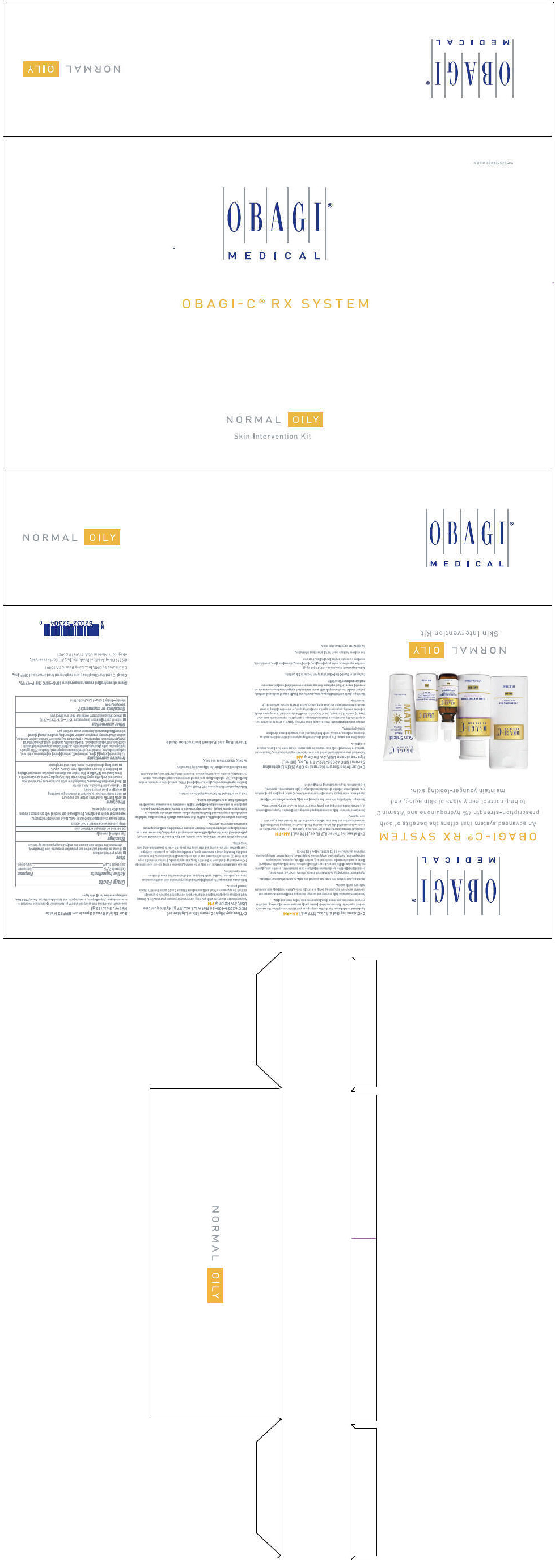 DRUG LABEL: OBAGI-C RX SYSTEM NORMAL-OILY
NDC: 62032-523 | Form: KIT | Route: TOPICAL
Manufacturer: OMP, INC.
Category: prescription | Type: HUMAN PRESCRIPTION DRUG LABEL
Date: 20130812

ACTIVE INGREDIENTS: HYDROQUINONE 40 mg/1 mL; HYDROQUINONE 40 mg/1 g; OCTINOXATE 75 mg/1 g; ZINC OXIDE 105 mg/1 g
INACTIVE INGREDIENTS: PROPYLENE GLYCOL; WATER; ASCORBIC ACID; SODIUM LAURYL SULFATE; PROPYLENE CARBONATE; ALCOHOL; DIPROPYLENE GLYCOL; EDETATE DISODIUM; PPG-2 MYRISTYL ETHER PROPIONATE; TROLAMINE SALICYLATE; SODIUM LAURYL SULFATE; CETYL ALCOHOL; GLYCERIN; LACTIC ACID; .ALPHA.-TOCOPHEROL ACETATE; ASCORBIC ACID; SODIUM METABISULFITE; WATER; METHYLPARABEN; PROPYLPARABEN; BUTYLATED HYDROXYTOLUENE; PHENYL TRIMETHICONE; CYCLOMETHICONE 5; WATER; GLYCERIN; PHENOXYETHANOL; PEG-10 DIMETHICONE (600 CST); PENTYLENE GLYCOL; STEARYL ALCOHOL; POLYOXYL 20 CETOSTEARYL ETHER; PHENYL TRIMETHICONE; PEG-40 STEARATE; DIMETHICONE; SODIUM DIHYDROXYCETYL PHOSPHATE; HYDROGENATED PALM GLYCERIDES; CITRIC ACID MONOHYDRATE; CETOSTEARYL ALCOHOL; .ALPHA.-TOCOPHEROL ACETATE; 1,2-HEXANEDIOL; CAPRYLYL GLYCOL; TROPOLONE; CHLORPHENESIN; XANTHAN GUM; POTASSIUM SORBATE; SODIUM BENZOATE; TETRAHEXYLDECYL ASCORBATE; UBIDECARENONE; EDETATE DISODIUM; METHYLISOTHIAZOLINONE; HYDROXYETHYL ACRYLATE/SODIUM ACRYLOYLDIMETHYL TAURATE COPOLYMER (45000 MPA.S AT 1%); SQUALANE; POLYSORBATE 60; SODIUM POLYACRYLATE (2500000 MW)

OBAGI-C® RX SYSTEM NORMAL-OILY
SKIN INTERVENTION KIT

C-Cleansing Gel 6 fl. oz. (177 mL.) AM+PM

A gel-based facial cleanser that clarifies and prepares your skin for absorption of the system's product ingredients. This concentrated cleanser gently removes excess oil, makeup, and other everyday impurities, and rinses clean, leaving your skin feeling fresh and clear.

Directions

Use twice daily, morning and evening. Massage a small amount of cleanser and lukewarm water onto skin, rubbing gently in a circular motion. Rinse completely with lukewarm water and gently pat dry.

Warnings

Avoid getting into eyes. For external use only.

Keep out of reach of children.

Ingredients

water (aqua), sodium laureth sulfate, sodium lauroyl oat amino acids, cocamidopropyl betaine, aloe barbadensis leaf juice (aloe barbadensis), ascorbic acid, glycerin, medicago sativa (alfalfa) extract, borago officinalis extract, chamomilla recutita (matricaria) flower extract (chamomilla recutita extract), sodium chloride, saponins, xanthan gum, phenoxyethanol, methylparaben, ethylparaben, butylparaben, propylparaben, isobutylparaben, fragrance (parfum), red 33 (CI 17200), yellow 5 (CI 19140)

C-Balancing Toner 6.7 fl. oz. (198 mL.) AM+PM

Specifically formulated for normal to oily skin, the C-Balancing Toner adjusts your skin's pH balance. As an essential step after cleansing, this alcohol-free, non-drying toner thoroughly removes impurities and dead skin cells to prepare the skin for the next step in your skin care regimen. s.

Directions

Use twice daily, in the morning and evening after cleansing. Pump a small amount (3-4 pumps) onto a cotton pad and gently wipe over entire face. Let air dry. Do not rinse.

Warnings

Avoid getting into eyes. For external use only.

Keep out of reach of children.

Ingredients

water (aqua), hamamelis virginiana (witch hazel) water, propylene glycol, sodium pca, benzalkonium chloride, aloe barbadensis leaf juice (aloe barbadensis), panthenol, polyquaternium-10, phenoxyethanol, methylparaben

C-Clarifying Serum Normal to Oily (Skin Lightening Serum) NDC 62032-122-10 1 fl. oz. (30 mL.) Hydroquinone USP, 4% Rx Only AM

Antioxidant serum containing Vitamin C and prescription-strength hydroquinone. This patented formulation for normal to oily skin reduces the appearance of dark spots for a lighter, brighter complexion.

Indications and usage

The gradual bleaching of hyperpigmented skin conditions such as chloasma, melasma, freckles, senile lentigines, and other unwanted areas of melanin hyperpigmentation.

Dosage and administration

Use once daily in the morning. Apply 5-7 drops to the entire face, or as directed by your skin care physician. Massage in gently. If no improvement is seen after three (3) months of treatment, use of this product should be discontinued. Sun exposure should be limited by using a sunscreen agent, a sun blocking agent, or protective clothing to cover bleached skin when using and after using this product in order to prevent darkening from reoccurring.

Warnings

Avoid contact with eyes, nose, mouth, or lips. In case of accidental contact, patient should rinse eyes thoroughly with water and contact physician. Sunscreen use is an essential aspect of hydroquinone therapy because even minimal sunlight exposure sustains melanocytic activity.

DESCRIPTION

Each gram of Obagi-C Rx C-Clarifying Serum Normal to Oily contains:

Active Ingredient

Hydroquinone USP, 4% (40 mg/g)

Inactive Ingredients

water, propylene glycol, alcohol denat., dipropylene glycol, ascorbic acid, propylene carbonate, sodium lauryl sulfate, fragrance

See enclosed Package Insert for full prescribing information.

Rx ONLY. FOR EXTERNAL USE ONLY.

C-Therapy Night Cream (Skin Lightener) NDC 62032-105-36 Net wt. 2 oz. (57 g.) Hydroquinone USP, 4% Rx Only PM

A rich moisturizer that works while you sleep to renew and rejuvenate your skin. The C-Therapy Night Cream is uniquely formulated with prescription-strength hydroquinone to gradually diminish the appearance of dark spots and delivers Vitamins C and E during the skin's nightly renewal process.

Indications and usage

The gradual bleaching of hyperpigmented skin conditions such as chloasma, melasma, freckles, senile lentigines, and other unwanted areas of melanin hyperpigmentation.

Dosage and Administration

Use daily in the evening. Dispense a small amount (approximately 1-2 pea-sized drops) and apply to the entire face. Massage in gently. If no improvement is seen after three (3) months of treatment, use of this product should be discontinued. Sun exposure should be limited by using a sunscreen agent, a sun blocking agent, or protective clothing to cover bleached skin when using and after using this product in order to prevent darkening from reoccurring.

Warnings

Avoid contact with eyes, nose, mouth, or lips. In case of accidental contact, patient should rinse eyes thoroughly with water and contact physician. Sunscreen use is an essential aspect of hydroquinone therapy because even minimal sunlight exposure sustains melanocytic activity.

Contains sodium metabisulfite, a sulfite that may cause allergic-type reactions including anaphylactic symptoms and life-threatening or less severe asthmatic episodes in certain susceptible people. The overall prevalence of sulfite sensitivity in the general population is unknown and probably low. Sulfite sensitivity is seen more frequently in asthmatic than in nonasthmatic people.

DESCRIPTION

Each gram of Obagi-C Rx C-Therapy Night Cream contains:

Active Ingredient

Hydroquinone USP, 4% (40 mg/g)

Inactive Ingredients

water, glycerin, cetyl alcohol, PPG-2 myristyl ether propionate, sodium lauryl sulfate, TEA-salicylate, lactic acid, phenyl trimethicone, tocopheryl acetate, sodium metabisulfite, ascorbic acid, methylparaben, disodium EDTA, propylparaben, saponins, BHT

See enclosed Package Insert for full prescribing information.

Rx ONLY. FOR EXTERNAL USE ONLY.

Travel Bag and Patient Instruction Guide

Sun Shield Broad Spectrum SPF 50 Matte Net wt. 3 oz. (85 g)

This sunscreen combines UVB absorption and UVA protection in an elegant matte finish that is non-comedogenic, hypoallergenic, non-acnegenic, and dermatologist tested. Sheer, PABA free, and fragrance free for all skin types.

Drug Facts

ACTIVE INGREDIENT

Active ingredients | Purpose
Octinoxate 7.5% | Sunscreen
Zinc Oxide 10.5% | Sunscreen

Uses

- helps prevent sunburn
- if used as directed with other sun protection measures (see Directions), decreases the risk of skin cancer and early skin aging caused by the sun

Warnings

For external use only

Do not use on damaged or broken skin

Stop use and ask a doctor if rash occurs

When using this product keep out of eyes. Rinse with water to remove.

Keep out of reach of children. If swallowed, get medical help or contact a Poison Control Center right away.

Directions

- apply liberally 15 minutes before sun exposure
- use a water resistant sunscreen if swimming or sweating
- reapply at least every 2 hours
- children under 6 months: Ask a doctor
- Sun Protection Measures. Spending time in the sun increases your risk of skin cancer and early skin aging. To decrease this risk, regularly use a sunscreen with a Broad Spectrum SPF value of 15 or higher and other sun protection measures including:
  - limit time in the sun, especially from 10 a.m.–2 p.m.
  - wear long-sleeved shirts, pants, hats, and sunglasses

Inactive ingredients

1,2 hexanediol, caprylyl glycol, ceteareth-20, cetearyl alcohol, chlorphenesin, citric acid, cyclopentasiloxane, dimethicone, dimethicone crosspolymer-3, disodium EDTA, glycerin, hydrogenated palm glycerides, hydroxyethyl acrylate/sodium acryloyldimethyl taurate copolymer, methylisothiazolinone, PEG-40 stearate, pentylene glycol, phenoxyethanol, phenyl trimethicone, polysilicone-11, polysorbate 60, potassium sorbate, sodium benzoate, sodium dihydroxycetyl phosphate, sodium polyacrylate, squalane, stearyl alcohol, tetrahexyldecyl ascorbate, tropolone, water, xanthan gum

Other information

- store at controlled room temperature: 15°C–25°C (59°F–77°F)
- protect this product from excessive heat and direct sun

Questions or comments?

1.800.636.7546
Monday–Friday 9 a.m.–4 p.m. Pacific Time

Store at controlled room temperature 15°C–25°C (59°F–77°F).

Obagi-C and the Obagi logo are registered trademarks of OMP, Inc.

Distributed by OMP, Inc., Long Beach, CA 90806

©2012 Obagi Medical Products, Inc. All rights reserved.
obagi.com Made in USA 41502111Z 5021

PRINCIPAL DISPLAY PANEL - Kit Carton

NDC # 62032-523-04

OBAGI®
MEDICAL

OBAGI-C® RX SYSTEM

NORMAL OILY

Skin Intervention Kit